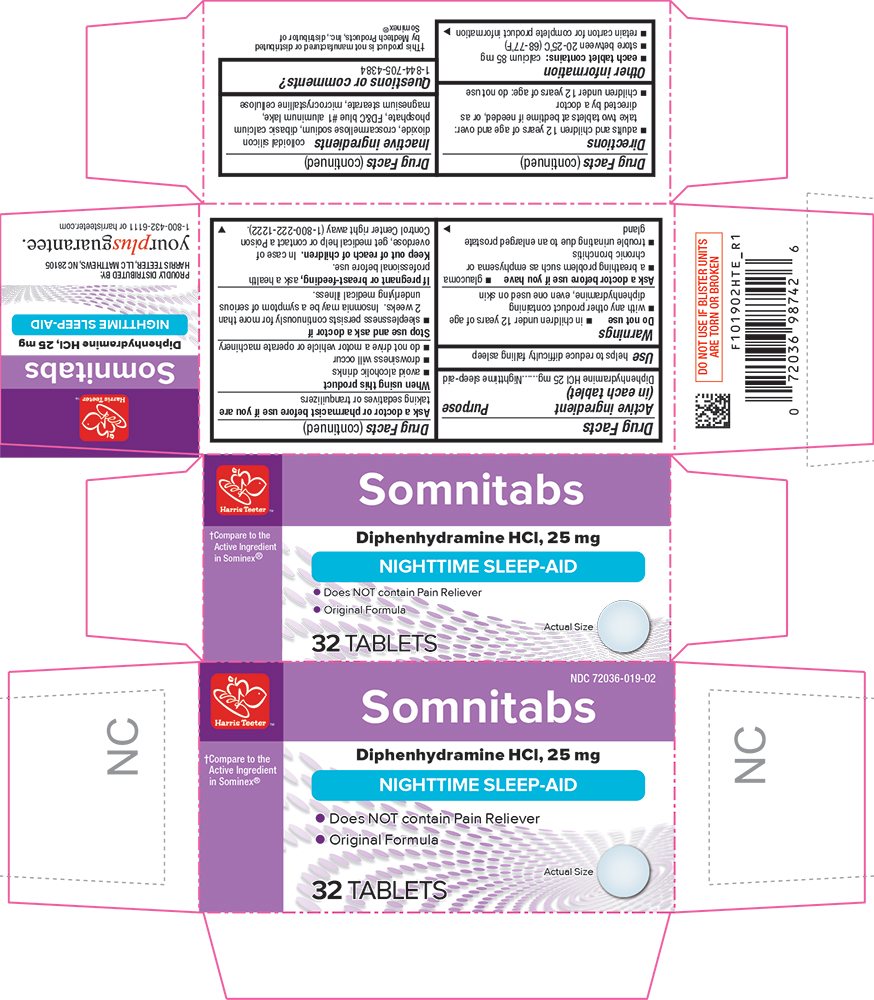 DRUG LABEL: Somnitabs
NDC: 72036-019 | Form: TABLET
Manufacturer: HARRIS TEETER
Category: otc | Type: HUMAN OTC DRUG LABEL
Date: 20250520

ACTIVE INGREDIENTS: DIPHENHYDRAMINE HYDROCHLORIDE 25 mg/1 1
INACTIVE INGREDIENTS: SILICON DIOXIDE; CROSCARMELLOSE SODIUM; CALCIUM PHOSPHATE, DIBASIC, ANHYDROUS; FD&C BLUE NO. 1; MAGNESIUM STEARATE; CELLULOSE, MICROCRYSTALLINE

HTE - 1019 - 2025-0520

Drug Facts

Active ingredient (in each tablet)

Diphenhydramine HCl 25 mg

Purpose

Nighttime sleep-aid

Use

helps to reduce difficulty falling asleep

Warnings

Do not use

- in children under 12 years of age
- with any other product containing diphenhydramine, even one used on skin

Ask a doctor before use if you have

- glaucoma
- a breathing problem such as emphysema or chronic bronchitis
- trouble urinating due to an enlarged prostate gland

Ask a doctor or pharmacist before use if you aretaking sedatives or tranquilizers

When using this productavoid alcoholic drinks

Stop use and ask a doctor ifsleeplessness persists continuously for more than 2 weeks. Insomnia may be a symptom of serious underlying medical illness.

PREGNANCY OR BREAST FEEDING

If pregnant or breast-feeding,ask a health professional before use.

Keep out of reach of children.

In case of overdose, get medical help or contact a Poison Control Center right away.

Directions

- adults and children 12 years of age and over: take 2 tablets at bedtime if needed, or as directed by a doctor

Other information

- each tablet contains: calcium 85 mg
- store at room temperature 15°-30°C (59°-86°F)
- retain carton for complete product information

Inactive ingredients

colloidal silicon dioxide, croscarmellose sodium, dibasic calcium phosphate, FD&C blue #1, magnesium stearate, microcrystalline cellulose

Questions or comments?

1-844-705-4384

PRINCIPAL DISPLAY PANEL

Harris Teeter™

Somnitabs

Compare to the Active Ingredient in Sominex®

Diphenhydramine HCl, 25 mg

NIGHTTIME SLEEP-AID

•Does NOT contain Pain Reliever

• Original Formula

32 TABLETS